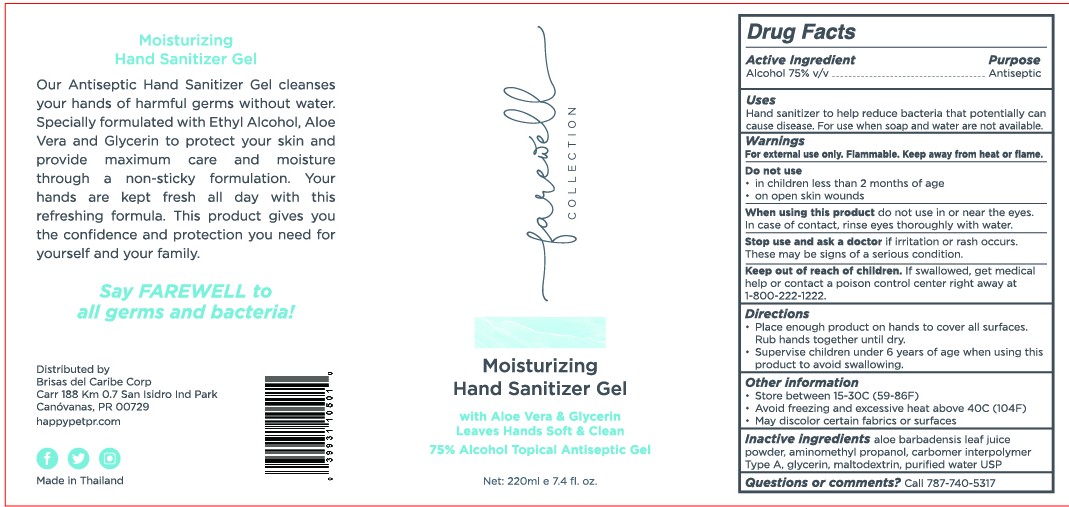 DRUG LABEL: Farewell Collection
NDC: 81892-111 | Form: GEL
Manufacturer: Paveemol Company Limited
Category: otc | Type: HUMAN OTC DRUG LABEL
Date: 20210620

ACTIVE INGREDIENTS: ALCOHOL 75 mL/100 mL
INACTIVE INGREDIENTS: GLYCERIN; CARBOMER INTERPOLYMER TYPE A (55000 CPS); WATER; AMINOMETHYLPROPANOL; ALOE VERA LEAF; MALTODEXTRIN

Paveemol-Brisas-220 mL Alcohol Gel

Active Ingredient(s)

Alcohol 75% v/v. Purpose: Antiseptic

Purpose

Antiseptic, Hand Sanitizer

Use

Hand Sanitizer to help reduce bacteria that potentially can cause disease. For use when soap and water are not available.

Warnings

For external use only. Flammable. Keep away from heat or flame

Do not use

- in children less than 2 months of age
- on open skin wounds

When using this product keep out of eyes, ears, and mouth. In case of contact with eyes, rinse eyes thoroughly with water.
Stop use and ask a doctor if irritation or rash occurs. These may be signs of a serious condition.
Keep out of reach of children. If swallowed, get medical help or contact a Poison Control Center right away.

Stop use and ask a doctor if irritation or rash occurs. These may be signs of a serious condition.

Keep out of reach of children. If swallowed, get medical help or contact a Poison Control Center right away 1 800-222-1222

Directions

- Place enough product on hands to cover all surfaces. Rub hands together until dry.
- Supervise children under 6 years of age when using this product to avoid swallowing.

Other information

- Store between 15-30C (59-86F)
- Avoid freezing and excessive heat above 40C (104F)
- May discolor certain fabrics or surfaces

Inactive ingredients

aloe barbadensis leaf juice powder, aminomethyl propanol, carbomer interpolymer type A, glycerin, maltodextrin, purified water USP

Package Label - Principal Display Panel

220 mL NDC:81892-111-12